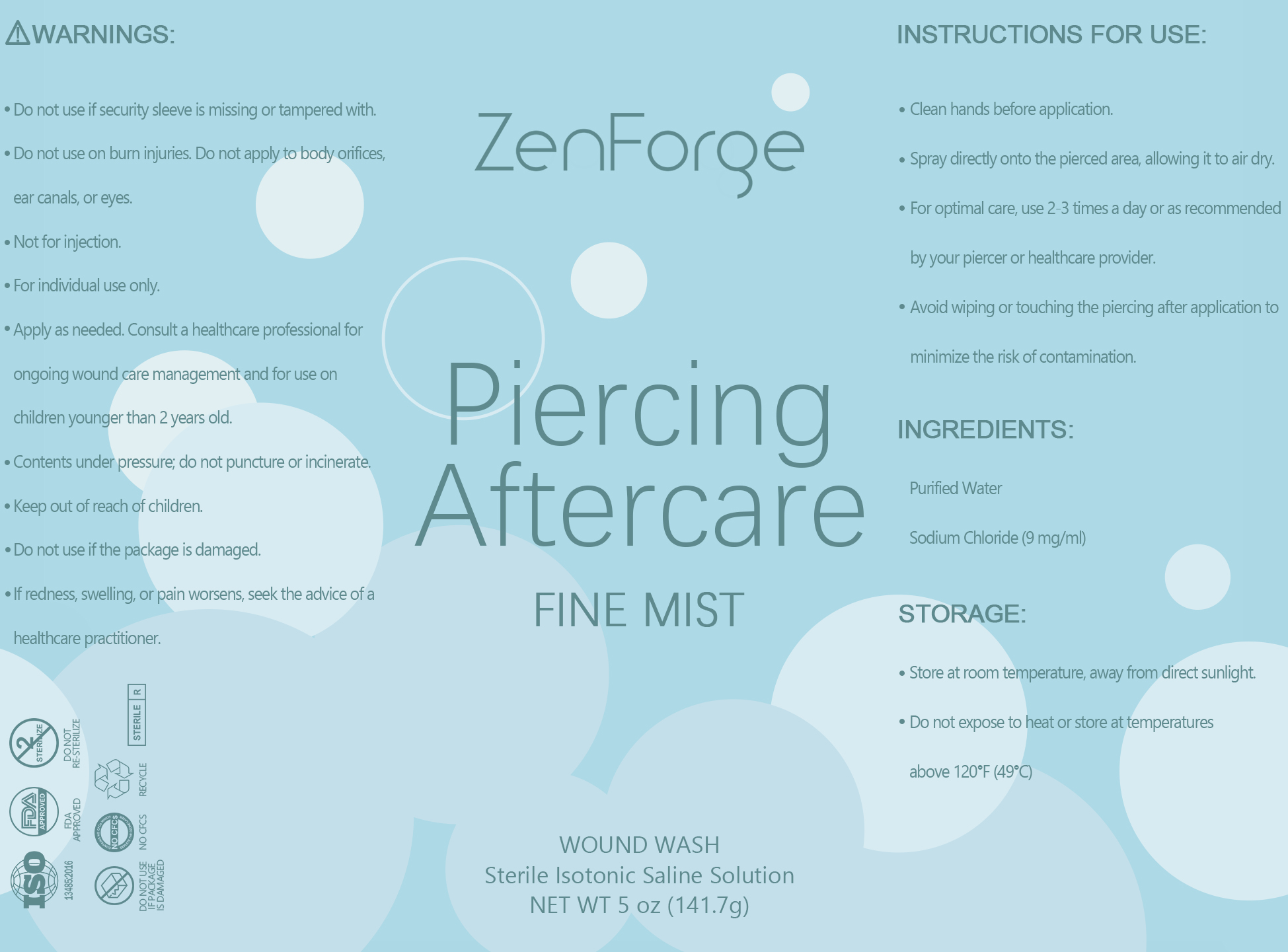 DRUG LABEL: Sterile Isotonic Saline Solution
NDC: 84939-001 | Form: INJECTION, SOLUTION
Manufacturer: Qingdao TOPN Import & Export Co.,Ltd
Category: homeopathic | Type: HUMAN OTC DRUG LABEL
Date: 20241113

ACTIVE INGREDIENTS: WATER 0.01 mg/1 mL
INACTIVE INGREDIENTS: ISOTONIC SODIUM CHLORIDE SOLUTION

INACTIVE INGREDIENT

Purified Water

ACTIVE INGREDIENT

Sodium Chloride

WARNINGS SECTION

PURPOSE SECTION

DOSAGE AND ADMINISTRATION

9 mg/ml

KEEP OUT OF REACH OF CHILDREN SECTION

INDICATIONS AND USAGE

Clean hands before application.
Spray directly onto the pierced area, allowing it to air dry.
For optimal care, use 2-3 times a day or as recommended by your piercer or healthcare provider.
Avoid wiping or touching the piercing after application to minimize the risk of contamination.